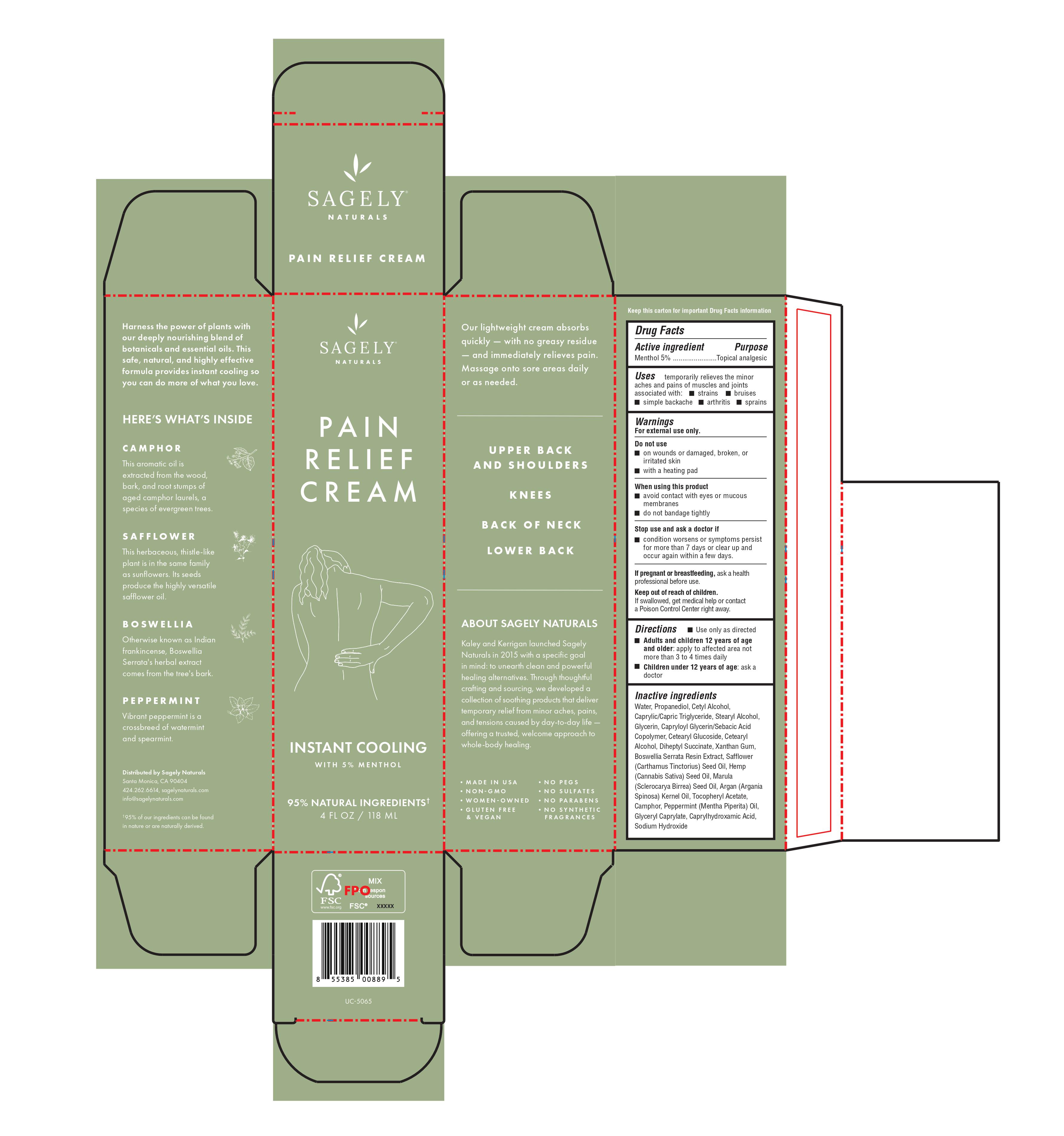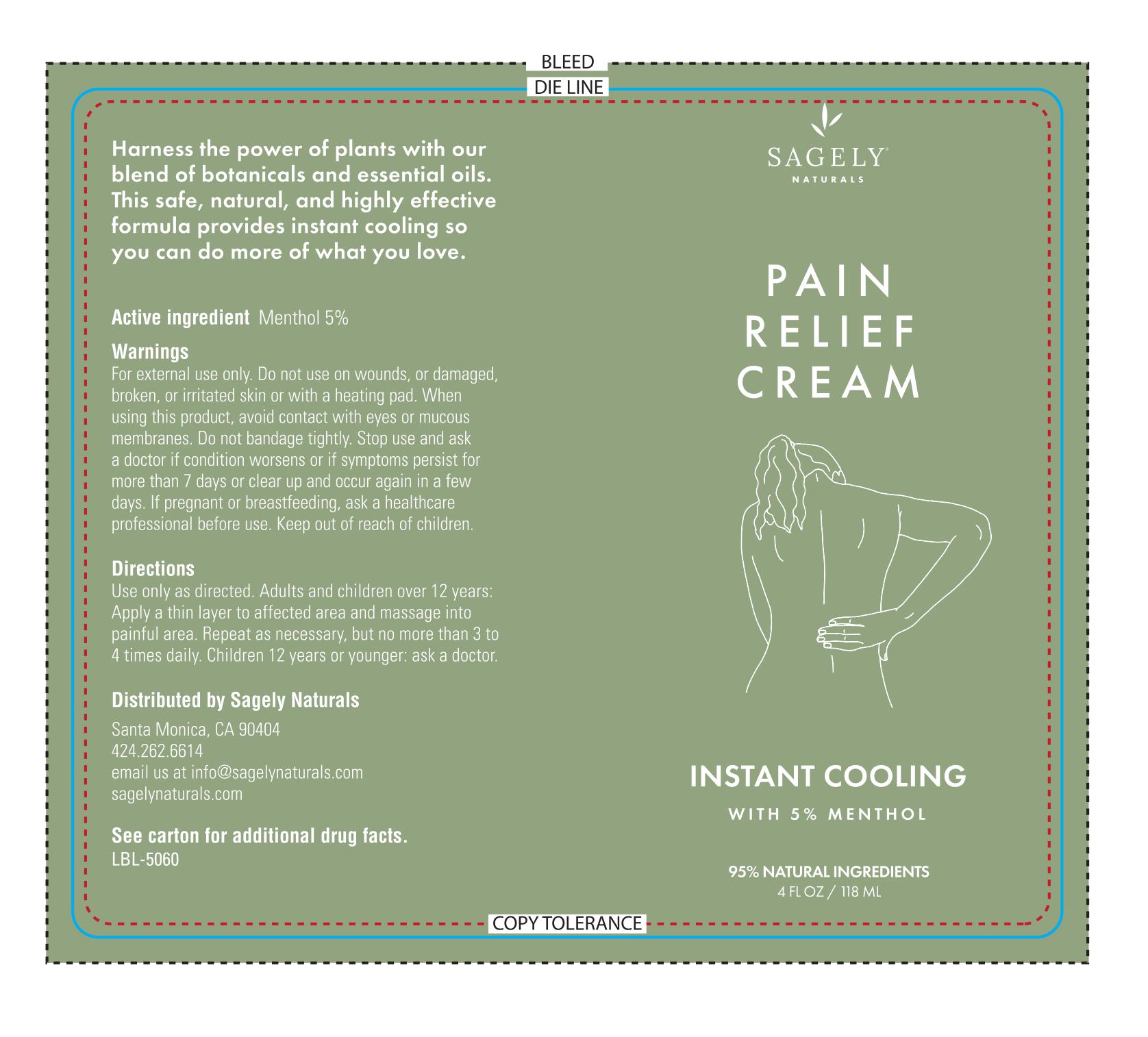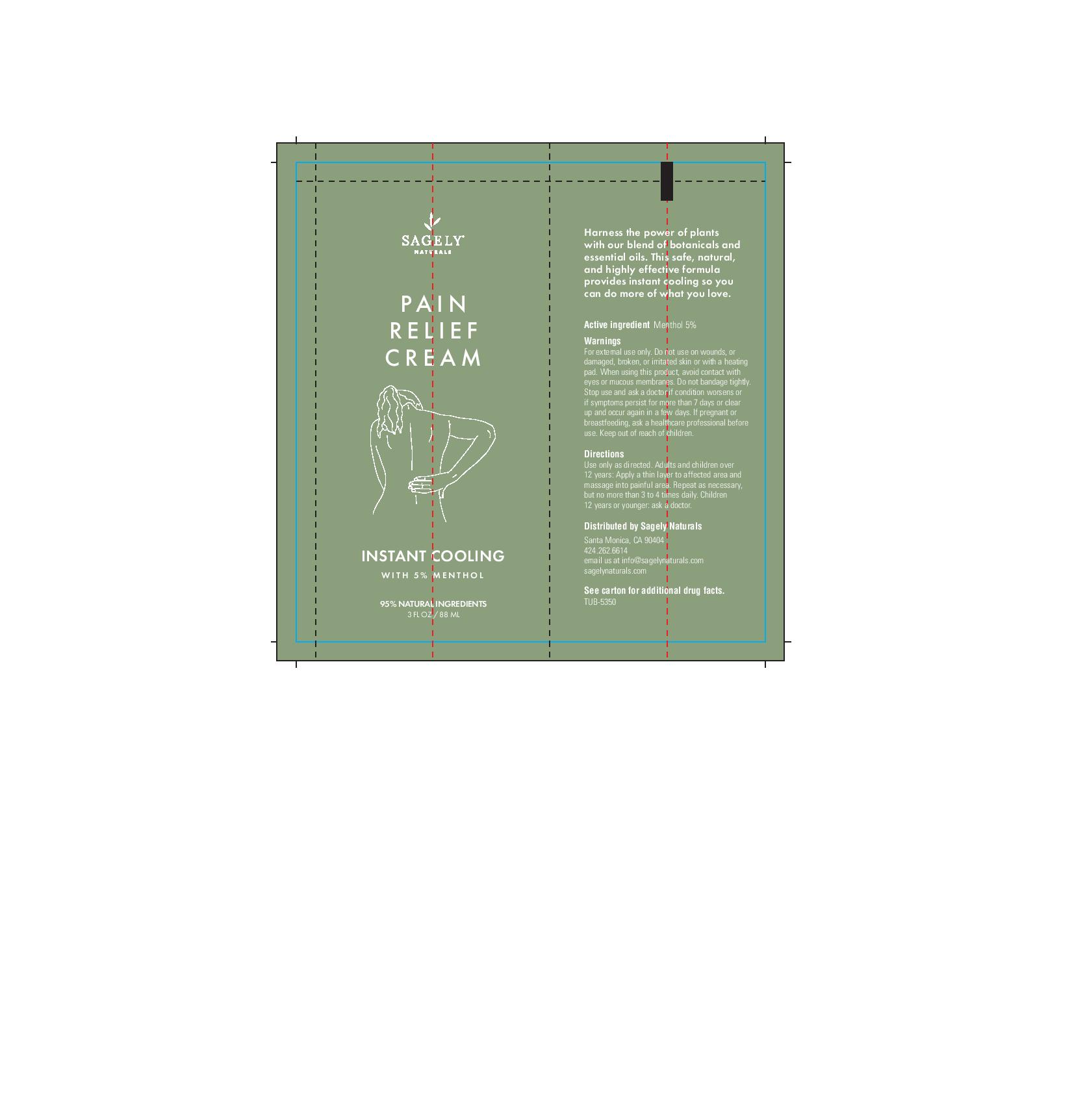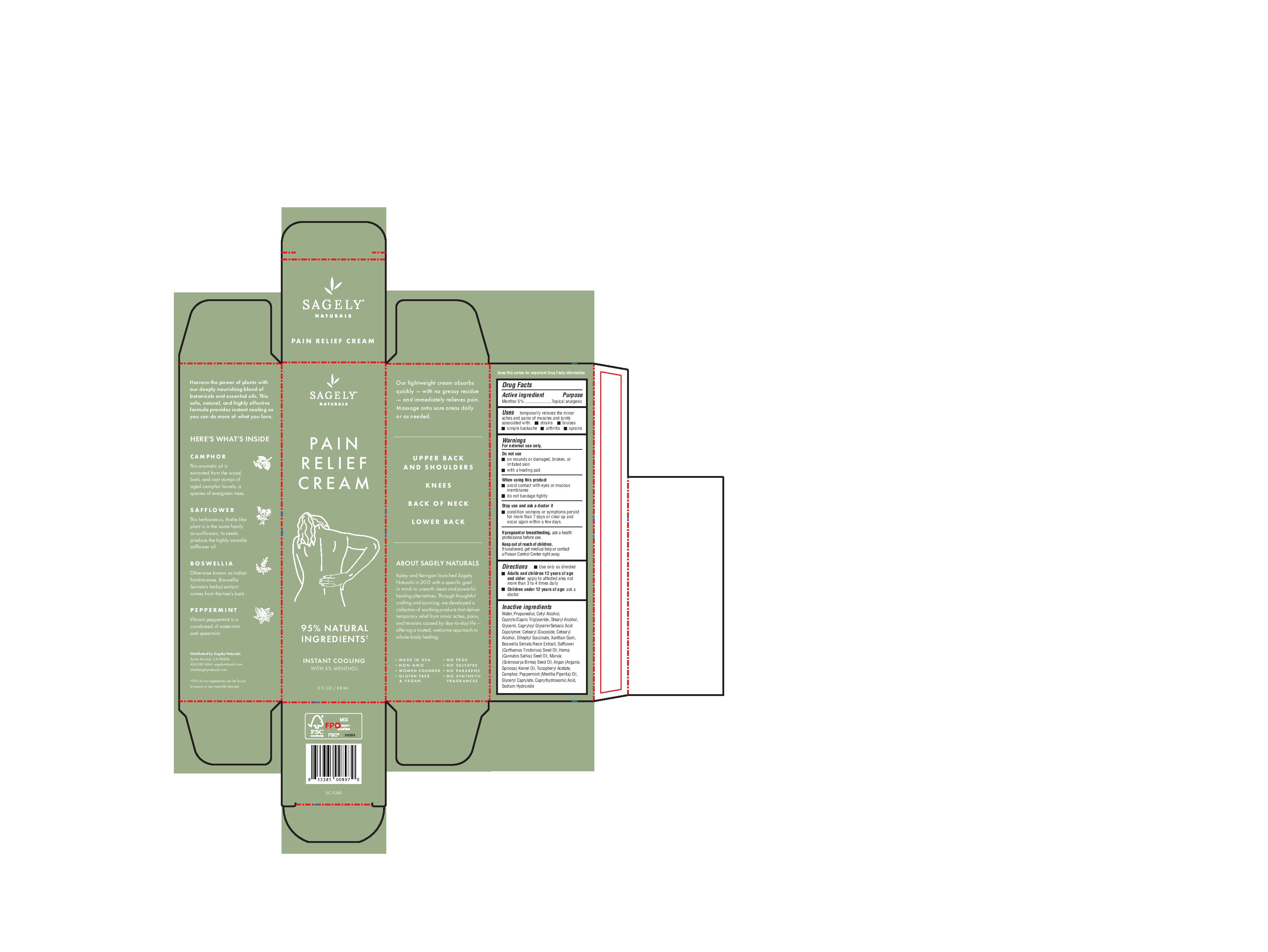 DRUG LABEL: Pain Relief Cream
NDC: 82075-410 | Form: CREAM
Manufacturer: Sagely Enterprises Inc.
Category: otc | Type: HUMAN OTC DRUG LABEL
Date: 20211119

ACTIVE INGREDIENTS: MENTHOL 5 g/100 g
INACTIVE INGREDIENTS: GLYCERIN; BOSWELLIA SERRATA RESIN OIL; SAFFLOWER OIL; CETEARYL GLUCOSIDE; XANTHAN GUM; .ALPHA.-TOCOPHEROL ACETATE; CAMPHOR (NATURAL); CANNABIS SATIVA SEED OIL; ARGAN OIL; GLYCERYL CAPRYLATE; CAPRYLHYDROXAMIC ACID; PROPANEDIOL; CAPRYLOYL GLYCERIN/SEBACIC ACID COPOLYMER (2000 MPA.S); CETOSTEARYL ALCOHOL; DIHEPTYL SUCCINATE; STEARYL ALCOHOL; WATER; CETYL ALCOHOL; MEDIUM-CHAIN TRIGLYCERIDES; SCLEROCARYA BIRREA SEED OIL; PEPPERMINT OIL; SODIUM HYDROXIDE

Pain Relief Cream

Active ingredient

Menthol 5%

Purpose

Menthol 5%.................Topical analgesic

Uses

temporarily relieves the minor aches and pains of muscles and joints associated with:

- strains
- bruises
- simple backache
- arthritis
- sprains

Warnings

For external use only.

Do not use

- on wounds or damaged, broken, or irritated skin
- with a heating pad

When using this product

- avoid contact with eyes or mucous membranes
- do not bandage tightly

Stop use and ask a doctor if

- condition worsens or symptoms persist for more than 7 days or clear up and occur again within a few days.

PREGNANCY OR BREAST FEEDING

If pregnant or breastfeeding, ask a health professional before use.

Keep out of reach of children. If swallowed, get medical help or contact a Poison Control Center right away.

Directions

- Use only as directed
- Adults and children 12 years of age and older: apply to affected area not more than 3 to 4 times daily
- Children under 12 years of age: ask a doctor

Inactive ingredients

Water, Propanediol, Cetyl Alcohol, Caprylic/Capric Triglyceride, Stearyl Alcohol, Glycerin, Capryloyl Glycerin/Sebacic Acid Copolymer, Cetearyl Glucoside, Cetearyl Alcohol, Diheptyl Succinate, Xanthan Gum, Boswellia Serrata Resin Extract, Safflower (Carthamus Tinctorius) Seed Oil, Hemp (Cannabis Sativa) Seed Oil, Marula (Sclerocarya Birrea) Seed Oil, Argan (Argania Spinosa) Kernel Oil, Tocopheryl Acetate, Camphor, Peppermint (Mentha Piperita) Oil, Glyceryl Caprylate, Caprylhydroxamic Acid, Sodium Hydroxide

PACKAGE LABEL

Sagely Naturals

Pain Relief Cream

Instant Cooling

With 5% Menthol

95% Natural Ingredients

4 FL OZ / 118 ML